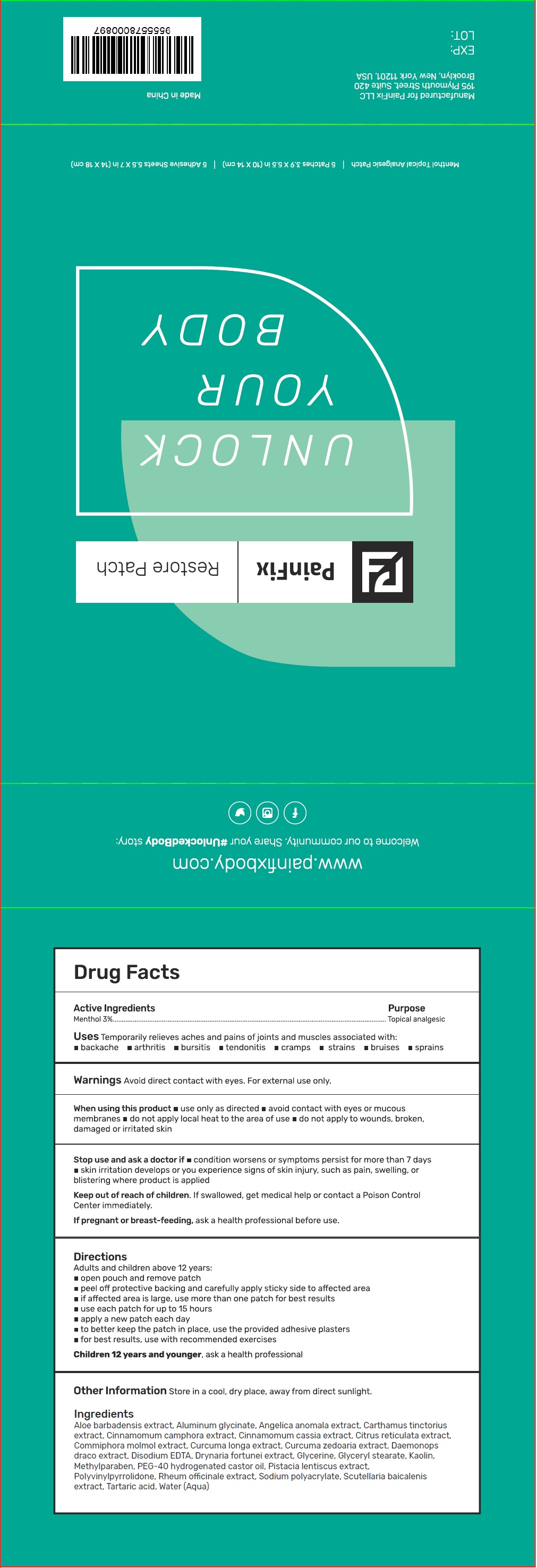 DRUG LABEL: PainFix Restore
NDC: 72749-000 | Form: PATCH
Manufacturer: PainFix LLC
Category: otc | Type: HUMAN OTC DRUG LABEL
Date: 20190218

ACTIVE INGREDIENTS: MENTHOL 30 mg/1 mL
INACTIVE INGREDIENTS: GLYCERIN; GLYCERYL MONOSTEARATE; KAOLIN; METHYLPARABEN; POLYOXYL 40 HYDROGENATED CASTOR OIL; TARTARIC ACID; WATER; DIHYDROXYALUMINUM AMINOACETATE ANHYDROUS; TURMERIC; EDETATE DISODIUM ANHYDROUS

PainFix Restore Patch

Active Ingredients

Menthol 3%

Purpose

`Topical analgesic

Uses

Temporarily relieves aches and pains of joints and muscles associated with: • backache • arthritis • bursitis • tendonits • cramps • strains • bruises • sprains

Warnings

Avoid direct contact with eyes. For external use only.

When using this product

• use only as directed • avoid contact with eyes or mucous membranes • do not apply local heat to the area of use • do not apply to wounds, broken, damaged or irritated skin

Stop use and ask a doctor if

• condition worsens or symptoms persist for more than 7 days • skin irritation develops or you experience signs of skin injury, such as pain, swelling, or blistering where product is applied

Keep out of reach of children.

If swallowed, get medical help or contact a Poison Control Center immediately.

If pregnant or breast-feeding,

ask a health professional before use.

Directions

Adults and children above 12 years:

- open pouch and remove patch
- peel off protective backing and carefully apply sticky side to affected area
- if affected area is large, use more than one patch for best results
- use each patch for up to 15 hours
- apply a new patch each day
- to better keep the patch in place, use the provided adhesive plasters
- for best results, use with recommended exercises

Children 12 years and younger, ask a health professional

Other Information

Store in a cool, dry place, away from direct sunlight.

Ingredients

Aloe barbadensis extract, Aluminum glycinate, Angelica anomala extract, Carthamus tinctorius extract, Cinnamomum camphora extract, Cinnamomum cassia extract, Citrus reticulata extract, Commiphora molmol extract, Curcuma longa extract, Curcuma zedoaria extract, Daemonops draco extract, Disodium EDTA, Drynaria fortunei extract, Glycerine, Glyceryl stearate, Kaolin, Methylparaben, PEG-40 hydrogenated castor oil, Pistacia lentiscus extract, Polyvinylpyrrolidone, Rheum officinale extract, Sodium polyacrylate, Scutellaria baicalenis extract, Tartaric acid, Water (Aqua)